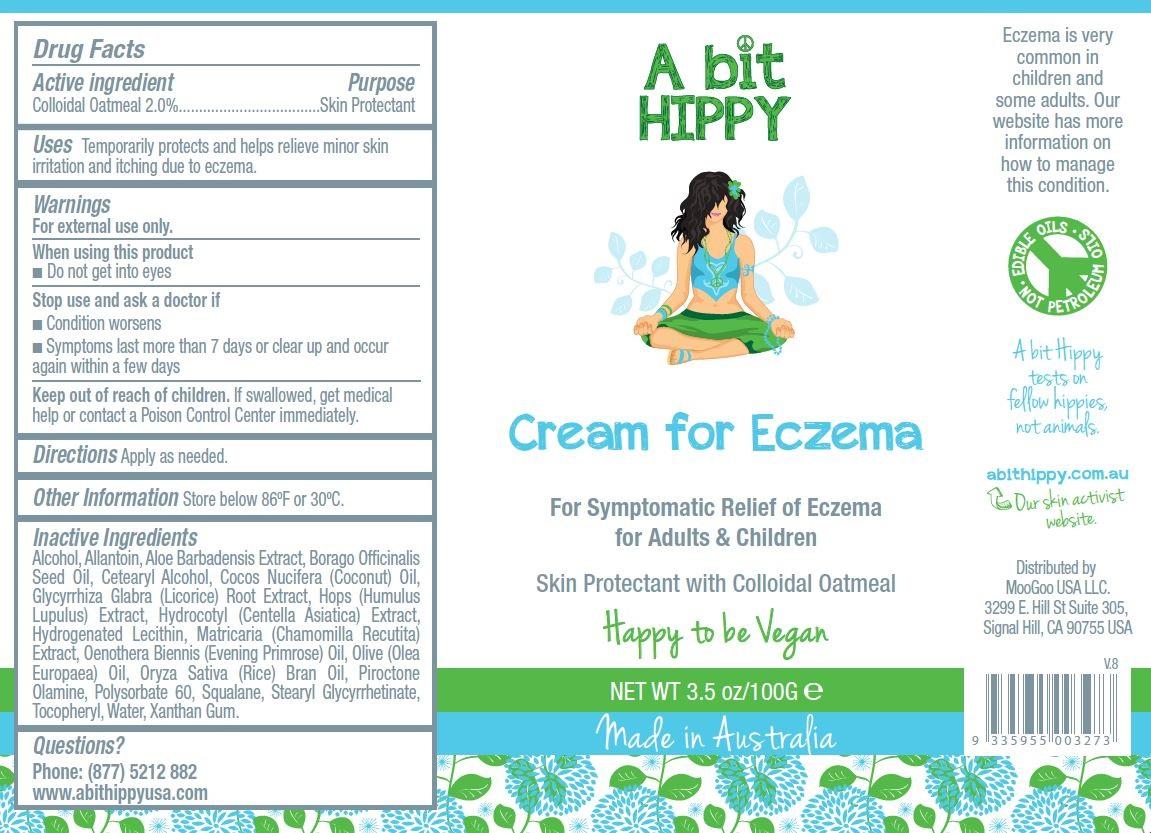 DRUG LABEL: A Bit Hippy
NDC: 69788-002 | Form: CREAM
Manufacturer: MooGoo USA LLC
Category: otc | Type: HUMAN OTC DRUG LABEL
Date: 20151026

ACTIVE INGREDIENTS: OATMEAL 2.5 g/100 g
INACTIVE INGREDIENTS: WATER; ALMOND OIL; CETOSTEARYL ALCOHOL; POLYSORBATE 60; PEG-150 STEARATE; STEARETH-20; OLIVE OIL; SQUALANE; AVENA SATIVA TOP; ALOE VERA LEAF; MATRICARIA RECUTITA FLOWERING TOP; CENTELLA ASIATICA LEAF; PIROCTONE OLAMINE; ALLANTOIN; TOCOPHEROL; XANTHAN GUM; GLYCERYL CAPRYLATE; PHYTATE SODIUM; HUMULUS LUPULUS WHOLE

Active Ingredient Purpose

Colloidal Oatmeal 2.0% .................. Skin Protectant

PURPOSE

Uses Temporarily protects and helps relieve minor skin irritation and itching due to eczema.

Keep out of reach of children. If swallowed, get medical help or contact a Poison Control Center immediately.

INDICATIONS AND USAGE

A Bit Hippy

Cream for Eczema

For Symptomatic Relief of Eczema for Adults & Children

Skin Protectant with Colloidal Oatmeal

Eczema is very common in children and some adults. Our website has more information on how to manage this condition.

A Bit Hippy tests on fellow hippies, not animals.

abithippy.com.au

Directions

Apply as needed.

Warnings

For external use only. When using this product

- do not get into eyes

Stop use and ask a doctor if

- condition worsens
- symptoms last more than 7 days or clear up and occur again within a few days

Inactive Ingredients

alcohol, allantoin, aloe barbadensis extract, borago officinalis seed oil, cetearyl alcohol, cocos nucifera (coconut) oil, glycyrrhiza glabra (licorice) root extract, hops (humulus lupulus) extract, hydrocotyl (centella asiatica) extract, hydrogenated lecithin, matricaria (chamomilla recutita) extract, oenothera biennis (evening primrose) oil, olive (olea europaea) oil, oryza sativa (rice) bran oil, piroctone olamine, polysorbate 60, squalane, stearyl glycyrrhetinate, tocopheryl, water, xanthan gum.